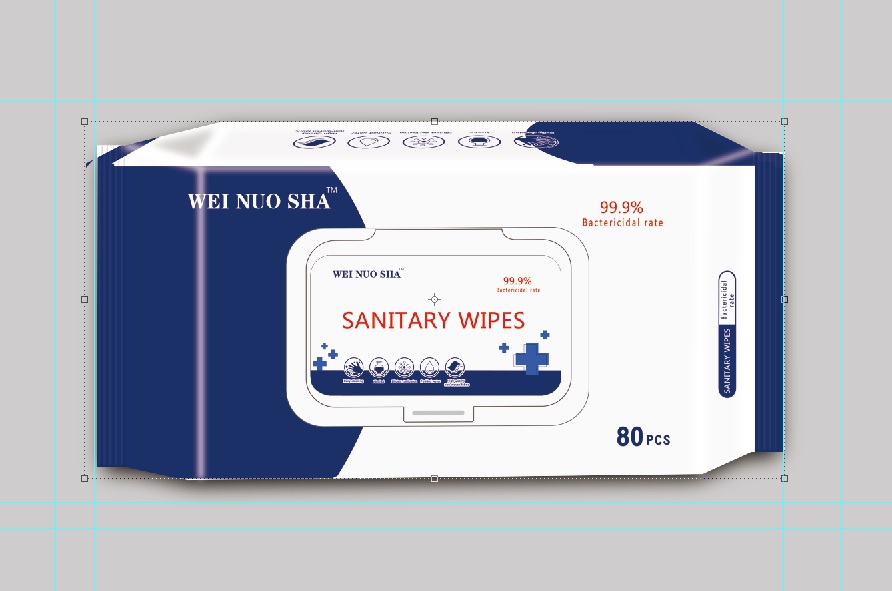 DRUG LABEL: Instant Hand Sanitizeing Wipe
NDC: 79539-002 | Form: CLOTH
Manufacturer: Shandong Yayun Sanitary Products Co., Ltd.
Category: otc | Type: HUMAN OTC DRUG LABEL
Date: 20241121

ACTIVE INGREDIENTS: PROPYLENE GLYCOL 1.2 g/1 1
INACTIVE INGREDIENTS: GLYCERIN; ALOE BARBADENSIS LEAF EXTRACT; EDETATE DISODIUM; PHENOXYETHANOL; BENZALKONIUM CHLORIDE; WATER; .ALPHA.-TOCOPHEROL ACETATE; CETYLPYRIDINIUM CHLORIDE; SULFURYL FLUORIDE; SODIUM CITRATE; CHAMOMILE

Instant Hand Sanitizeing Wipe

Instant Hand Sanitizeing Wipe

Active Ingredient(s)

BENZALKONIUM CHLORIDE 1.2g/pcs. Purpose: Antiseptic

Purpose

Antiseptic, Instant Hand Sanitizeing Wipe

Use

Instant Hand Sanitizeing Wipe to help reduce bacteria that potentially can cause disease. For use when soap and water are not available.

Warnings

For external use only. Flammable. Keep away from heat or flame

Do not use

- in children less than 2 months of age
- on open skin wounds

When using this product keep out of eyes, ears, and mouth. In case of contact with eyes, rinse eyes thoroughly with water.
Stop use and ask a doctor if irritation or rash occurs. These may be signs of a serious condition.
Keep out of reach of children. If swallowed, get medical help or contact a Poison Control Center right away.

Stop use and ask a doctor if irritation or rash occurs. These may be signs of a serious condition.

Keep out of reach of children. If swallowed, get medical help or contact a Poison Control Center right away.

Directions

- Wipe the surface of the skin and let it dry naturally.
- Supervise children under 6 years of age when using this product to avoid swallowing.

Other information

- Store between 15-30C (59-86F)
- Avoid freezing and excessive heat above 40C (104F)

Inactive ingredients

WATER
SODIUM CITRATE
Compound double-stranded quaternary ammonium salt